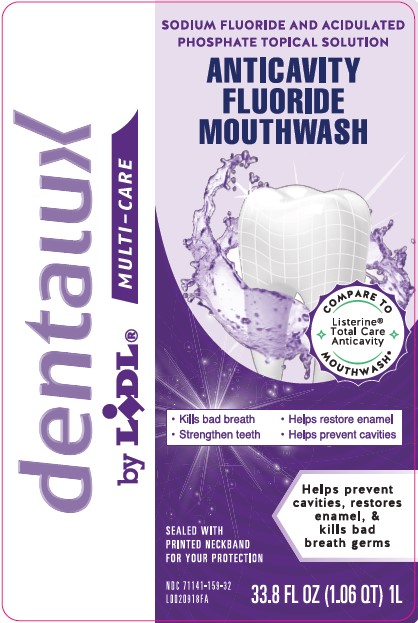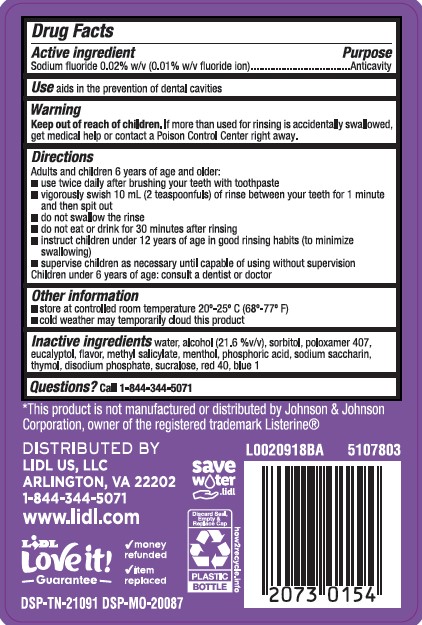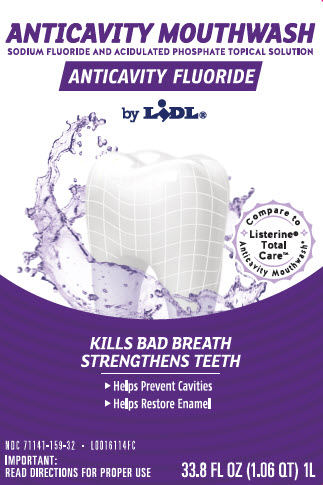 DRUG LABEL: Anticavity Fluoride Rinse
NDC: 71141-159 | Form: MOUTHWASH
Manufacturer: Lidl US, LLC
Category: otc | Type: HUMAN OTC DRUG LABEL
Date: 20260204

ACTIVE INGREDIENTS: SODIUM FLUORIDE 0.1 mg/1 mL
INACTIVE INGREDIENTS: WATER; ALCOHOL; SORBITOL; POLOXAMER 407; EUCALYPTOL; METHYL SALICYLATE; MENTHOL; PHOSPHORIC ACID; SACCHARIN SODIUM; THYMOL; SODIUM PHOSPHATE, DIBASIC, ANHYDROUS; SUCRALOSE; FD&C RED NO. 40; FD&C BLUE NO. 1

Dentalux_Lidl 163.005/163AF-AG
Anticavity Fluoride Rinse

Active Ingredient

Sodium fluoride 0.02% w/v (0.01% fluoride ion)

Purpose

Antcavity

Use

aids in the prevention of dental cavities

Warnings

for this product

Keep out of reach of children.

If more than used for rinsing is accidentally swallowed, get medical help or contact a Poison Control Center right away.

Directions

Adults and children 6 years of age and older:

- use twice daily after brushing your teeth with a toothpaste
- vigorously swish 10 ml (2 teaspoonfuls) of rinse between your teeth for 1 minute and then spit it out
- do not swallow the rinse
- do not eat or drink for 30 minutes after rinsing
- instruct children under 12 years of age in good rinsing habits (to minimize swallowing)
- supervise children as necessary until capable of using without supervision

children under 6 years of age: consult a dentist or doctor

Other information

- store at controlled room temperature 20⁰ - 25⁰ C (68⁰ - 77⁰ F)
- cold weather may temporarily cloud this product

Inactive ingredients

water, alcohol (21.6 %v/v), sorbitol, poloxamer 407, eucalyptol, flavor, methyl salicylate, menthol, phosphoric acid, sodium saccharin, thymol, disodium phosphate, sucralose, red 40, blue 1

Questions?

Call 1-844-344-5071

Disclaimer

*This product is not manufactured or distributed by Johnson & Johnson Corporation, owner of the registered trademark Listerine.

Adverse Reactions

DISTRIBUTED BY

Lidl US, LLC

Arlington, VA 22202

1-844-344-5071

www.Lidl.com

Lidl Love it! Guarantee

- money refunded
- item replaced

save water.lidl

how2recycle.info

Discard Seal, Empty & Replace Cap

Plastic Bottle

DSP-TN-21091 DSP-MO-20087

Principal display panel

ANTICAVITY MOUTHWASH

SODIUM FLUORIDE AND ACIDULATED PHOSPHATE TOPICAL SOLUTION

ANTICAVITY FLUORIDE

by LIDL

COMPARE TO LISTERINE TOTAL CARE ANTICAVITY MOUTHWASH

Kills Bad Breath and Strengthens Teeth to Help Prevent Cavities

- Helps restore enemal
- Helps prevent cavities

IMPORTANT: read directions for proper use

33.8 FL OZ (1.06 QT) 1L

principal display panel

dentalux

by LIDL®MUTLI-CARE

SODIUM FLUORIDE AND ACIDULATED PHOSPHATE TOPICAL SOLUTION

ANTIICAVITY FLUORIDE MOUTHWASH

Compare to Listerine®Total Care Anticavity Mouthwash*

- Kills bad breath
- Strengthen teeth
- Helps resotre enamel
- Helps prevent cavities

Sealed with printed neckband for your protection

Helps prevent cavities, restores enamel, & kills bad breath germs

NDC 71141-159-32

33.8 FL OZ (1.06 QT) 1L